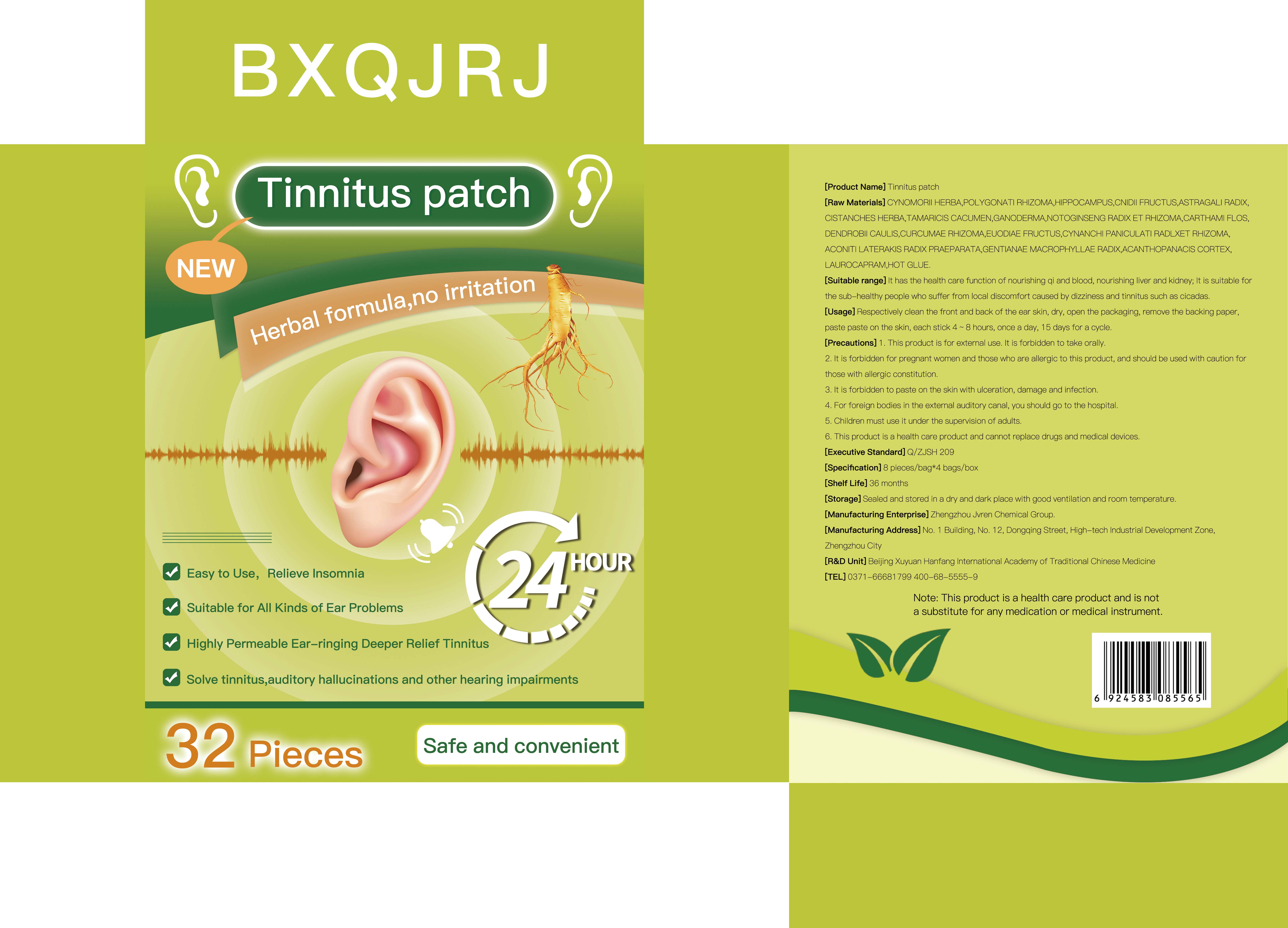 DRUG LABEL: Tinnitus patch
NDC: 52784-030 | Form: PATCH
Manufacturer: ZHENGZHOU GIANT BIOCHEMISTRY GROUP CO.,LTD
Category: homeopathic | Type: HUMAN OTC DRUG LABEL
Date: 20240119

ACTIVE INGREDIENTS: CYNOMORIUM SONGARICUM STEM 0.11 g/1 1
INACTIVE INGREDIENTS: CISTANCHE TUBULOSA STEM; TETRADIUM RUTICARPUM FRUIT; DENDROBIUM NOBILE STEM; CNIDIUM MONNIERI FRUIT; REISHI; TAMARIX CHINENSIS TOP; SAFFLOWER; CURCUMA AROMATICA ROOT; ASTRAGALUS MONGHOLICUS ROOT; ACONITUM CARMICHAELII WHOLE; GENTIANA MACROPHYLLA ROOT; LAUROCAPRAM; ELEUTHEROCOCCUS NODIFLORUS ROOT BARK; PANAX NOTOGINSENG ROOT; CYNANCHUM PANICULATUM ROOT; POLYGONATUM CYRTONEMA ROOT; HIPPOCAMPUS HISTRIX

Tinnitus patch

ACTIVE INGREDIENT

CYNOMORIUM SONGARICUM STEM

PURPOSE

Easy to Use，Relieve Insomnia
Suitable for All Kinds of Ear Problems
Highly Permeable Ear-ringing Deeper Relief Tinnitus
Solve tinnitus,auditory hallucinations and other hearing impairments

KEEP OUT OF REACH OF CHILDREN

Children must use it under the supervision of adults

INDICATIONS AND USAGE

lt has the health care function of nourishing gi and blood, nourishing liver and kidney; lt is suitable for the sub-healthy people who suffer from local discomfort caused by dizziness and tinnitus such as cicadas.

WARNINGS

1 . This product is for external use. lt is forbidden to take orally.
2. It is forbidden for pregnant women and those who are allergic to this product, and should be used with caution for those with allergic constitution.
3. lt is forbidden to paste on the skin with ulceration, damage and infection.
4. For foreign bodies in the external auditory canal, you should go to the hospital.
5. Children must use it under the supervision of adults.
6. This product is a health care product and cannot replace drugs and medical devices.

DOSAGE AND ADMINISTRATION

Respectively clean the front and back of the ear skin, dry, open the packaging, remove the backing paper,paste paste on the skin, each stick 4 ~ 8 hours, once a day, 15 days for a cycle.

STORAGE AND HANDLING

Sealed and stored in a dry and dark place with good ventilation and room temperature.
[Shelf Life] 36 months

DO NOT USE

1 . This product is for external use. lt is forbidden to take orally.
2. It is forbidden for pregnant women and those who are allergic to this product, and should be used with caution for those with allergic constitution.

INACTIVE INGREDIENT

POLYGONATI RHIZOMA
HIPPOCAMPUS
CNIDII FRUCTUS
ASTRAGALI RADIX
CISTANCHES HERBA
TAMARICIS CACUMEN
GANODERMA
NOTOGINSENG RADIX ET RHIZOMA
CARTHAMI FLOS
DENDROBII CAULIS
CURCUMAE RHIZOMA
EUODIAE FRUCTUS
CYNANCHI PANICULATI RADLXET RHIZOMA
ACONITI LATERAKIS RADIX PRAEPARATA
GENTIANAE MACROPHYLLAE RADIX
ACANTHOPANACIS CORTEX
LAUROCAPRAM